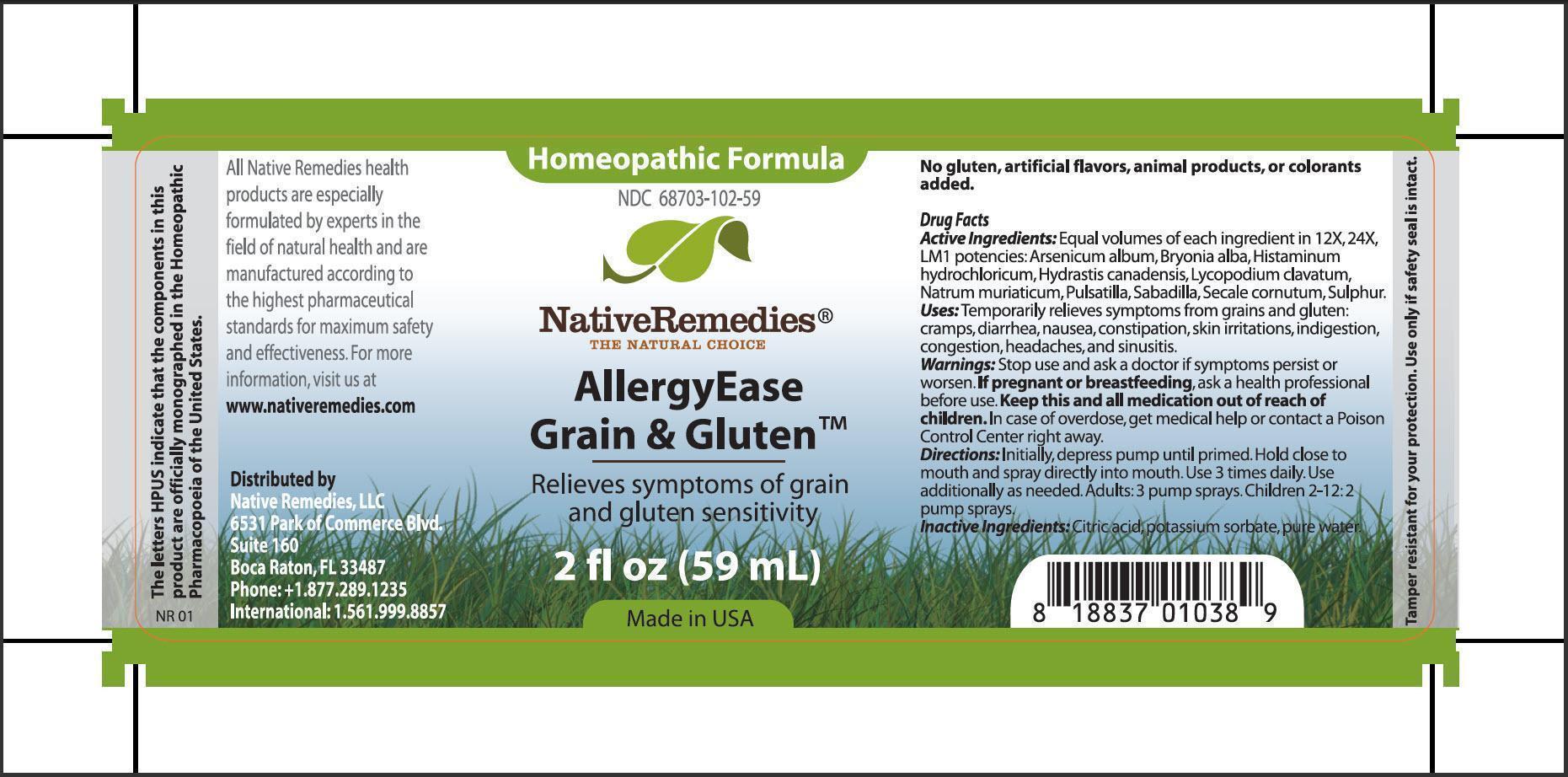 DRUG LABEL: AllergyEase Grain and Gluten
                
NDC: 68703-102 | Form: SPRAY
Manufacturer: Native Remedies, LLC
Category: homeopathic | Type: HUMAN OTC DRUG LABEL
Date: 20130605

ACTIVE INGREDIENTS: ARSENIC TRIOXIDE 12 [hp_X]/59 mL; BRYONIA ALBA ROOT 12 [hp_X]/59 mL; HISTAMINE DIHYDROCHLORIDE 12 [hp_X]/59 mL; GOLDENSEAL 12 [hp_X]/59 mL; LYCOPODIUM CLAVATUM SPORE 12 [hp_X]/59 mL; SODIUM CHLORIDE 12 [hp_X]/59 mL; PULSATILLA VULGARIS 12 [hp_X]/59 mL; SCHOENOCAULON OFFICINALE SEED 12 [hp_X]/59 mL; CLAVICEPS PURPUREA SCLEROTIUM 12 [hp_X]/59 mL; SULFUR 12 [hp_X]/59 mL
INACTIVE INGREDIENTS: CITRIC ACID MONOHYDRATE; POTASSIUM SORBATE; WATER

AllergyEase Grain and Gluten

PURPOSE

Relieves symptoms of grain and gluten sensitivity

Drug Facts
Active Ingredients: Equal volumes of each ingredient in 12X, 24X, LM1 potencies: Arsenicum album, Bryonia alba, Histaminum hydrochloricum, Hydrastis canadensis, Lycopodium clavatum, Natrum muriaticum, Pulsatilla, Sabadilla, Secale cornutum, Sulphur

INDICATIONS AND USAGE

Uses: Temporarily relieves symptoms from grains and gluten: cramps, diarrhea, nausea, constipation, skin irritations, indigestions, congestions, headaches, and sinusitis

WARNINGS

Warnings: Stop use and ask a doctor if symptoms persist or worsen

PREGNANCY OR BREAST FEEDING

If pregnant or breastfeeding, ask a health professional

KEEP OUT OF REACH OF CHILDREN

Keep this and all medication out of reach of children

OVERDOSAGE

In case of overdose, get medical help or contact a Poison Control Center right away

DOSAGE AND ADMINISTRATION

Directions: Initially, depress pump until primed. Hold close to mouth and spray directly into mouth. Use 3 times daily. Use additionally as needed. Adults: 3 pumps sprays. Children 2-12: 2 pumps sprays

Inactive Ingredients: Citric acid, potassium sorbate, pure water

PATIENT COUNSELING INFORMATION

The letter HPUS indicate that the components in this product are officially monographed in the Homeopathic Pharmacopoeia of the United States.

All Native Remedies health products are especially formulated by experts in the field of natural health and are manufactured according to the highest pharmaceutical standards for maximum safety and effectiveness. For more information, visit us at www.nativeremedies.com

Distributed by
Native Remedies, LLC
6531 Suite 160
Boca Raton, FL 33487
Phone:+1.877.289.1235
International:1.561.999.8857

No gluten, artificial flavors, animal products, or colorants added

STORAGE AND HANDLING

Tamper resistant for your protection. Use only if safety seal is intact